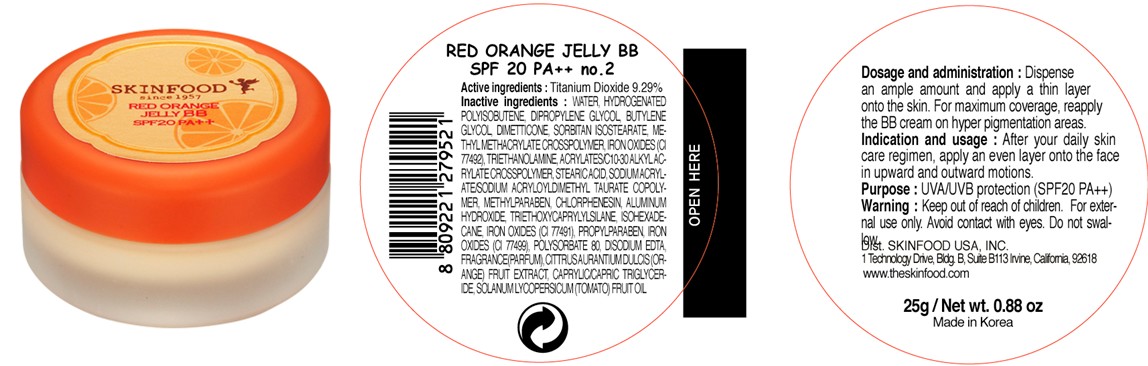 DRUG LABEL: RED ORANGE JELLY BB
NDC: 76214-043 | Form: CREAM
Manufacturer: SKINFOOD CO., LTD.
Category: otc | Type: HUMAN OTC DRUG LABEL
Date: 20111116

ACTIVE INGREDIENTS: TITANIUM DIOXIDE 2.32 g/25 g
INACTIVE INGREDIENTS: WATER; DIPROPYLENE GLYCOL; BUTYLENE GLYCOL; DIMETHICONE; TROLAMINE; STEARIC ACID; METHYLPARABEN; CHLORPHENESIN; ALUMINUM HYDROXIDE; TRIETHOXYCAPRYLYLSILANE; ISOHEXADECANE; PROPYLPARABEN; POLYSORBATE 80; EDETATE DISODIUM; ORANGE; MEDIUM-CHAIN TRIGLYCERIDES; TOMATO

Drug Facts

Active ingredient: TITANIUM DIOXIDE 9.29%

Inactive ingredients:
Water, Hydrogenated Polyisobutene, Dipropylene Glycol, Butylene Glycol, Dimethicone, Sorbitan Isostearate, Methyl Methacrylate Crosspolymer, Iron Oxides (CI 77492), Triethanolamine, Acrylates/C10-30 Alkyl Acrylate Crosspolymer, Stearic Acid, Sodium Acrylate/Sodium Acryloyldimethyl Taurate Copolymer, Methylparaben, Chlorphenesin, Iron Oxides (CI 77491), Aluminum Hydroxide, Triethoxycaprylylsilane, Isohexadecane, Iron Oxides (CI 77499), Propylparaben, Polysorbate 80, Disodium EDTA, Fragrance(Parfum), Citrus Aurantium Dulcis (Orange) Fruit Extract, Caprylic/Capric Triglyceride, Solanum Lycopersicum (Tomato) Fruit Oil

Purpose: UVA/UVB protection

Warnings:
For external use only.
Avoid contact with eyes.
Do not swallow.
Discontinue use if signs of irritation appear.

Keep out of reach of children:

Keep out of reach of children

Indication and usage:
After your daily skin care regimen, apply an even layer onto the face in upward and outward motions.

Dosage and administration:
Dispense an ample amount and apply a thin layer onto the skin.
For maximum coverage, reapply the BB cream on hyper pigmentation areas.